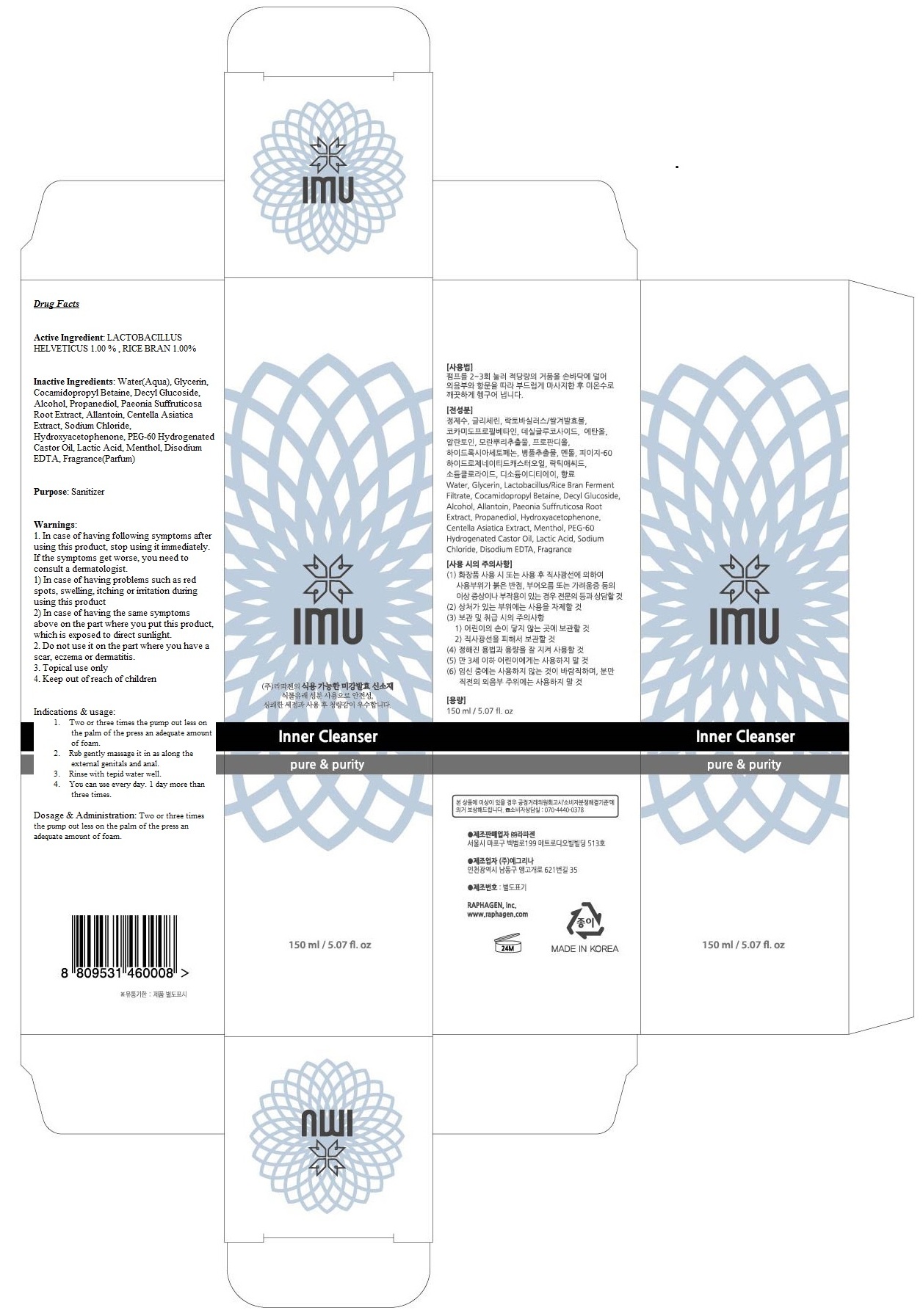 DRUG LABEL: IMU
NDC: 71125-010 | Form: AEROSOL, FOAM
Manufacturer: RAPHAGEN CO. LTD
Category: otc | Type: HUMAN OTC DRUG LABEL
Date: 20170112

ACTIVE INGREDIENTS: LACTOBACILLUS HELVETICUS 1.50 g/150 mL; RICE BRAN 1.50 g/150 mL
INACTIVE INGREDIENTS: Water; Glycerin

ACTIVE INGREDIENT

Active Ingredient: LACTOBACILLUS HELVETICUS 1.00 % , RICE BRAN 1.00%

INACTIVE INGREDIENT

Inactive Ingredients: Water(Aqua), Glycerin, Cocamidopropyl Betaine, Decyl Glucoside, Alcohol, Propanediol, Paeonia Suffruticosa Root Extract, Allantoin, Centella Asiatica Extract, Sodium Chloride, Hydroxyacetophenone, PEG-60 Hydrogenated Castor Oil, Lactic Acid, Menthol, Disodium EDTA, Fragrance(Parfum)

PURPOSE

Purpose: Sanitizer

WARNINGS

Warnings: 1. In case of having following symptoms after using this product, stop using it immediately. If the symptoms get worse, you need to consult a dermatologist. 1) In case of having problems such as red spots, swelling, itching or irritation during using this product 2) In case of having the same symptoms above on the part where you put this product, which is exposed to direct sunlight. 2. Do not use it on the part where you have a scar, eczema or dermatitis. 3. Topical use only 4. Keep out of reach of children

KEEP OUT OF REACH OF CHILDREN

INDICATIONS & USAGE

Indications & usage: 1. Two or three times the pump out less on the palm of the press an adequate amount of foam. 2. Rub gently massage it in as along the external genitals and anal. 3. Rinse with tepid water well. 4. You can use every day. 1 day more than three times.

DOSAGE & ADMINISTRATION

Dosage & Administration: Two or three times the pump out less on the palm of the press an adequate amount of foam.